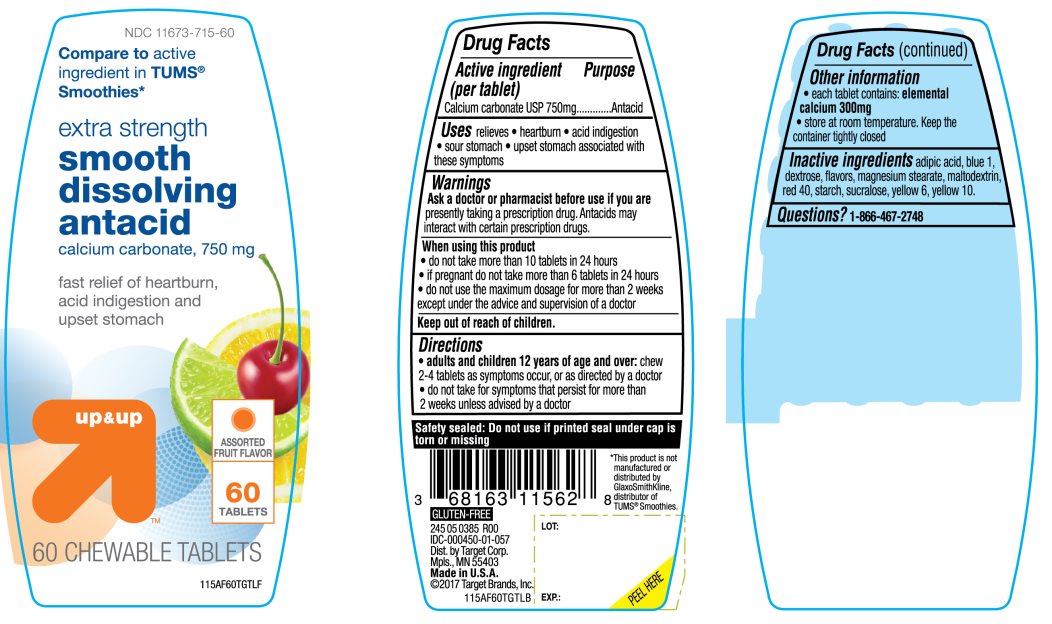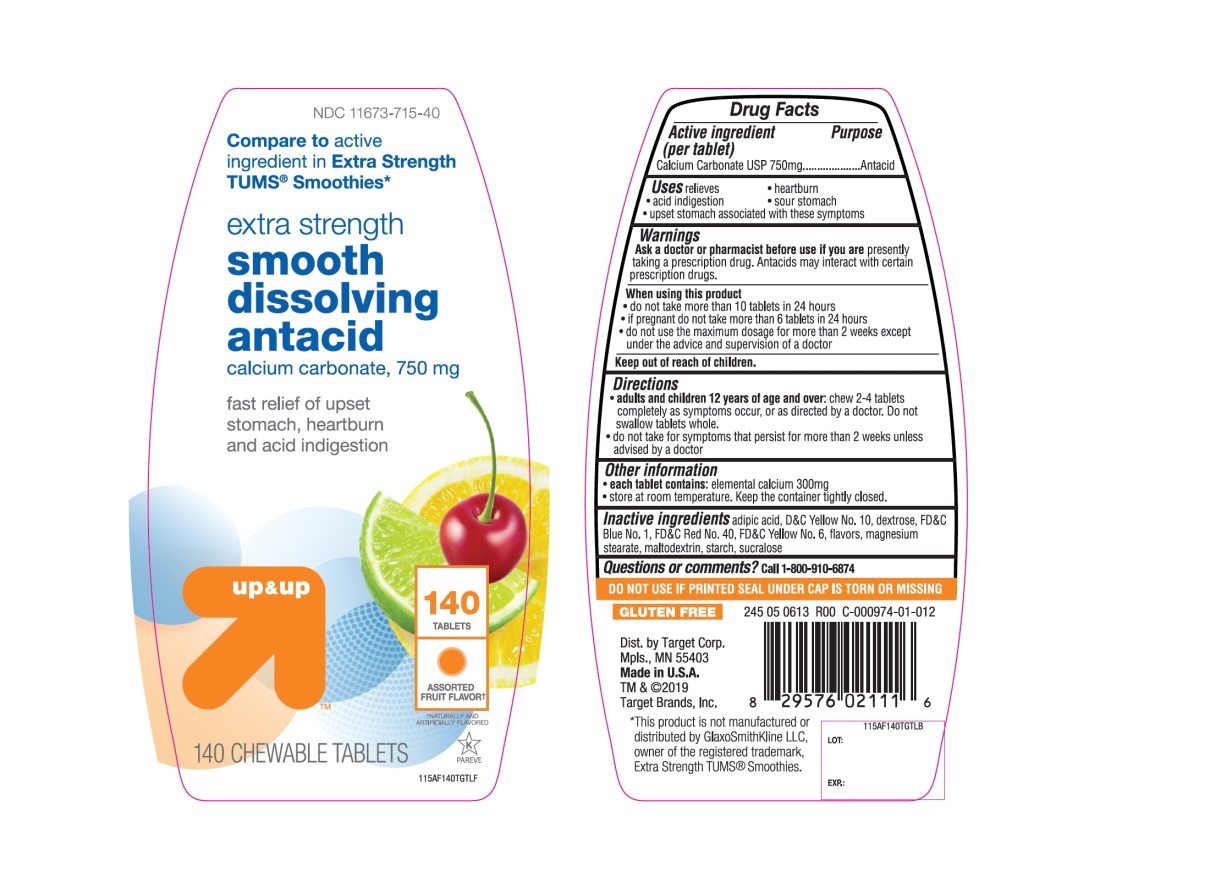 DRUG LABEL: up and up extra strength smooth dissolving antacid

NDC: 11673-715 | Form: TABLET, CHEWABLE
Manufacturer: Target corporation
Category: otc | Type: HUMAN OTC DRUG LABEL
Date: 20251104

ACTIVE INGREDIENTS: CALCIUM CARBONATE 750 mg/1 1
INACTIVE INGREDIENTS: ADIPIC ACID; D&C YELLOW NO. 10; DEXTROSE, UNSPECIFIED FORM; FD&C BLUE NO. 1; FD&C RED NO. 40; FD&C YELLOW NO. 6; MAGNESIUM STEARATE; MALTODEXTRIN; STARCH, CORN; SUCRALOSE

up and up extra strength smooth dissolving antacid

Active ingredient (per tablet)

Calcium Carbonate USP 750mg

Purpose

Antacid

Uses

relieves

- heartburn
- acid indigestion
- sour stomach
- upset stomach associated with these symptoms

Warnings

Ask a doctor or pharmacist before use if you arepresently taking a prescription drug. Antacids may interact with certain prescription drugs.

When using this product

- do not take more than 10 tablets in 24 hours
- if pregnant do not take more than 6 tablets in 24 hours
- do not use the maximum dosage for more than 2 weeks except under the advice and supervision of a doctor.

Directions

- adults and children 12 years of age and over:chew 2-4 tablets as symptoms occur, or as directed by a doctor
- do not take for symptoms that persist for more than 2 weeks unless advised by a doctor

Other information

- each tablet contains:elemental calcium 300mg
- store at room temperature. Keep the container tightly closed

Inactive ingredients

adipic acid, blue 1, dextrose, flavors, magnesium stearate, maltodextrin, red 40, starch, sucralose, yellow 6, yellow 10.

Safety sealed: Do not use if printed seal under cap is torn or missing

Questions

1-866-467-2748

Package/Label Principal Display Panel

Compare to active ingredient in TUMS®Smoothies*

extra strength

smooth dissolving antacid

calcium carbonate, 750 mg

fast relief of heartburn, acid indigestion and upset stomach

ASSORTED FRUIT FLAVOR

GLUTEN-FREE

245 05 0385 R00 IDC-000450-01-057

245 05 0613 R00 C-000974-01-012

Dist.by Target Corp.

Mpls., MN 55403

Made in U.S.A

©2017 Target Brands, Inc.

*This product is not manufactured or distributed by GlaxoSmithKline LLC, distributor of TUMS® Smoothies.

Package Label for 60 Chewable Tablets